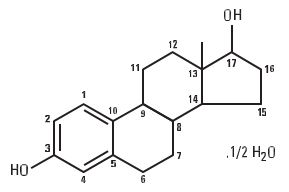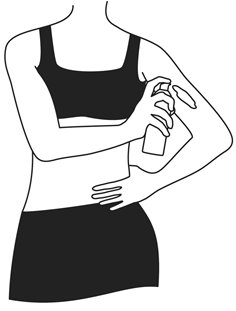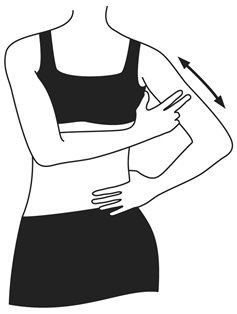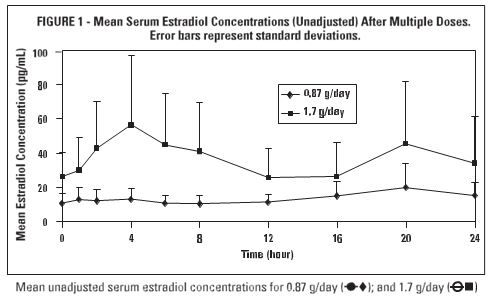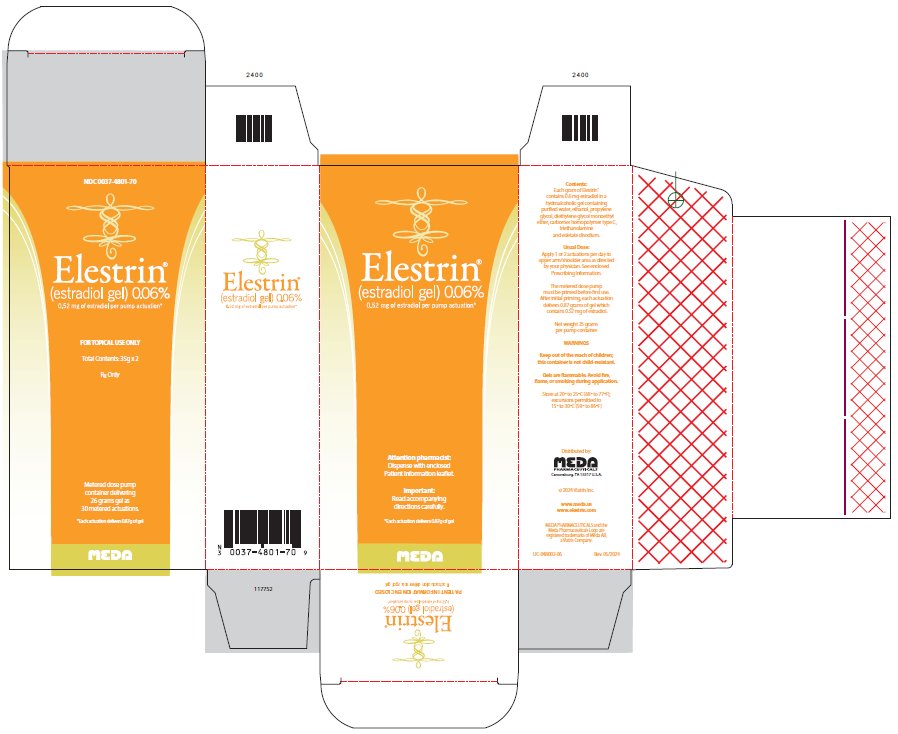 DRUG LABEL: ELESTRIN
NDC: 0037-4801 | Form: GEL, METERED
Manufacturer: Viatris Specialty LLC
Category: prescription | Type: HUMAN PRESCRIPTION DRUG LABEL
Date: 20231215

ACTIVE INGREDIENTS: ESTRADIOL 0.52 mg/0.87 g
INACTIVE INGREDIENTS: WATER; ALCOHOL; PROPYLENE GLYCOL; DIETHYLENE GLYCOL MONOETHYL ETHER; EDETATE DISODIUM; CARBOMER HOMOPOLYMER TYPE C (ALLYL PENTAERYTHRITOL CROSSLINKED); TROLAMINE

HIGHLIGHTS OF PRESCRIBING INFORMATION

These highlights do not include all the information needed to use ELESTRIN safely and effectively. See full prescribing information for ELESTRIN.
Elestrin® (estradiol gel), for topical use
Initial U.S. Approval: 1975

RECENT MAJOR CHANGES

Warnings and Precautions, Malignant Neoplasms (5.2) 12/2023

WARNING: ENDOMETRIAL CANCER, CARDIOVASCULAR DISORDERS, PROBABLE DEMENTIA and BREAST CANCER

See full prescribing information for complete boxed warning.

Estrogen-Alone Therapy

- There is an increased risk of endometrial cancer in a woman with a uterus who uses unopposed estrogens (5.2)
- Do not use estrogen-alone therapy should for the prevention of cardiovascular disease or dementia (5.1, 5.3)
- The Women’s Health Initiative (WHI) estrogen-alone substudy reported increased risks of stroke and deep vein thrombosis (DVT) (5.1)
- The WHI Memory Study (WHIMS) estrogen-alone ancillary study of WHI reported an increased risk of probable dementia in postmenopausal women 65 years of age and older (5.3)

Estrogen Plus Progestin Therapy

- Do not use estrogen plus progestin therapy for the prevention of cardiovascular disease or dementia (5.1, 5.3)
- The WHI estrogen plus progestin substudy reported increased risks of stroke, DVT, pulmonary embolism (PE), and myocardial infarction (MI) (5.1)
- The WHI estrogen plus progestin study reported increased risks of invasive breast cancer (5.2)
- The WHIMS estrogen plus progestin ancillary study of WHI reported an increased risk of probable dementia in postmenopausal women 65 years of age and older (5.3)

1 INDICATIONS AND USAGE

ELESTRIN is an estrogen indicated for the treatment of moderate to severe vasomotor symptoms due to menopause (1.1)

2 DOSAGE AND ADMINISTRATION

Start therapy with daily administration of one pump actuation to deliver 0.87 grams of gel providing 0.52 mg estradiol to the upper arm. Dosage adjustment should be guided by the clinical response (2.1)

3 DOSAGE FORMS AND STRENGTHS

Metered dose pump: 0.87 grams of gel per pump actuation delivers 0.52 mg of estradiol

4 CONTRAINDICATIONS

- Undiagnosed abnormal genital bleeding (4)
- Breast cancer or a history of breast cancer (4, 5.2)
- Estrogen-dependent neoplasia (4, 5.2)
- Active DVT, PE, or history of these conditions (4, 5.1)
- Active arterial thromboembolic disease (for example, stroke and MI) or a history of these conditions (4, 5.1)
- Known anaphylactic reaction or angioedema or hypersensitivity with ELESTRIN (4)
- Hepatic impairment or disease (4, 5.10)
- Protein C, protein S, or antithrombin deficiency, or other known thrombophilic disorders (4)

5 WARNINGS AND PRECAUTIONS

- Estrogens increase the risk of gallbladder disease (5.4)
- Discontinue estrogen if severe hypercalcemia, loss of vision, severe hypertriglyceridemia or cholestatic jaundice occurs (5.5, 5.6, 5.9, 5.10)
- Monitor thyroid function in women on thyroid replacement therapy (5.11, 5.21)

6 ADVERSE REACTIONS

The most common adverse reactions (≥ 5 percent) in any ELESTRIN treatment group are: breast tenderness, metrorrhagia, nasopharyngitis, and upper respiratory tract infections. (6.1)

To report SUSPECTED ADVERSE REACTIONS, contact Meda at 1-877-999-8401 or FDA at 1-800-FDA-1088 or www.fda.gov/medwatch

7 DRUG INTERACTIONS

- Inducers and/or inhibitors of CYP3A4 may affect estrogen drug metabolism and decrease or increase the estrogen plasma concentrations (7)

FULL PRESCRIBING INFORMATION

WARNING: ENDOMETRIAL CANCER, CARDIOVASCULAR DISORDERS, PROBABLE DEMENTIA and BREAST CANCER

Estrogen-Alone Therapy

Endometrial Cancer

There is an increased risk of endometrial cancer in a woman with a uterus who uses unopposed estrogens. Adding a progestin to estrogen therapy has been shown to reduce the risk of endometrial hyperplasia, which may be a precursor to endometrial cancer. Perform adequate diagnostic measures, including directed or random endometrial sampling when indicated, to rule out malignancy in postmenopausal women with undiagnosed, persistent or recurring abnormal genital bleeding [see Warnings and Precautions (5.2)].

Cardiovascular Disorders and Probable Dementia

Do not use estrogen-alone therapy for the prevention of cardiovascular disease or dementia [see Warnings and Precautions (5.1, 5.3), and Clinical Studies (14.2, 14.3)].

The Women’s Health Initiative (WHI) estrogen-alone substudy reported increased risks of stroke and deep vein thrombosis (DVT) in postmenopausal women (50 to 79 years of age) during 7.1 years of treatment with daily oral conjugated estrogens (CE) [0.625 mg] - alone, relative to placebo [see Warnings and Precautions (5.1), and Clinical Studies (14.2)].

The WHI Memory Study (WHIMS) estrogen-alone ancillary study of the WHI reported an increased risk of developing probable dementia in postmenopausal women 65 years of age or older during 5.2 years of treatment with daily CE (0.625 mg)-alone, relative to placebo. It is unknown whether this finding applies to younger postmenopausal women [see Warnings and Precautions (5.3), Use in Specific Populations (8.5), and Clinical Studies (14.3)].

Only daily oral 0.625 mg CE was studied in the estrogen-alone substudy of WHI. Therefore, the relevance of the WHI findings regarding adverse cardiovascular events and dementia to lower CE doses, other routes of administration, or other estrogen-alone products is not known. Without such data, it is not possible to definitively exclude these risks or determine the extent of these risks for other products. Discuss with your patient the benefits and risks of estrogen-alone therapy, taking into account her individual risk profile.

Prescribe estrogens with or without progestins at the lowest effective doses and for the shortest duration consistent with treatment goals and risks for the individual woman.

Estrogen Plus Progestin Therapy

Cardiovascular Disorders and Probable Dementia

Do not use estrogen plus progestin therapy for the prevention of cardiovascular disease or dementia [see Warnings and Precautions (5.1, 5.3), and Clinical Studies (14.2, 14.3)].

The WHI estrogen plus progestin substudy reported increased risks of DVT, pulmonary embolism (PE), stroke and myocardial infarction (MI) in postmenopausal women (50 to 79 years of age) during 5.6 years of treatment with daily oral CE (0.625 mg) combined with medroxyprogesterone acetate (MPA) [2.5 mg], relative to placebo [see Warnings and Precautions (5.1), and Clinical Studies (14.2)].

The WHIMS estrogen plus progestin ancillary study of the WHI reported an increased risk of developing probable dementia in postmenopausal women 65 years of age or older during 4 years of treatment with daily CE (0.625 mg) combined with MPA (2.5 mg), relative to placebo. It is unknown whether this finding applies to younger postmenopausal women [see Warnings and Precautions (5.3), Use in Specific Populations (8.5), and Clinical Studies (14.3)].

Breast Cancer

The WHI estrogen plus progestin substudy also demonstrated an increased risk of invasive breast cancer [see Warnings and Precautions (5.2), and Clinical Studies (14.2)].

Only daily oral 0.625 mg CE and 2.5 mg MPA were studied in the estrogen plus progestin substudy of WHI. Therefore, the relevance of the WHI findings regarding adverse cardiovascular events, dementia and breast cancer to lower CE plus other MPA doses, other routes of administration, or other estrogen plus progestin products is not known. Without such data, it is not possible to definitively exclude these risks or determine the extent of these risks for other products. Discuss with your patient the benefits and risks of estrogen plus progestin therapy, taking into account her individual risk profile.

Prescribe estrogens with or without progestins at the lowest effective doses and for the shortest duration consistent with treatment goals and risks for the individual woman.

2 DOSAGE AND ADMINISTRATION

Generally, when estrogen is prescribed for a postmenopausal woman with a uterus, consider addition of a progestin to reduce the risk of endometrial cancer.

Generally, a woman without a uterus does not need to take a progestin in addition to her estrogen therapy. In some cases, however, hysterectomized women who have a history of endometriosis may need a progestin [see Warnings and Precautions (5.2), (5.14)].

Use estrogen-alone, or in combination with a progestin, at the lowest effective dose and for the shortest duration consistent with treatment goals and risks for the individual woman. Reevaluate postmenopausal women periodically as clinically appropriate to determine if treatment is still necessary.

ELESTRIN is applied onto the skin in a thin layer. The recommended area of application is the upper arm to shoulder (approximately 320 cm^2).

2.1 Treatment of Moderate to Severe Vasomotor Symptoms due to Menopause

ELESTRIN is applied once daily to the upper arm for the treatment of moderate to severe vasomotor symptoms due to menopause using a metered-dose pump which delivers 0.87 grams of estradiol gel (0.52 mg estradiol) per actuation (1 pump).

Start therapy with one pump per day (0.87 grams per day, which contains 0.52 mg of estradiol).

Make dosage adjustments based on clinical response.

3 DOSAGE FORMS AND STRENGTHS

ELESTRIN is available in a metered dose pump which delivers 0.52 mg of estradiol in 0.87 grams of gel per pump actuation.

4 CONTRAINDICATIONS

ELESTRIN is contraindicated in women with any of the following conditions:

- Undiagnosed abnormal genital bleeding [see Warnings and Precautions (5.2)].
- Breast cancer or a history of breast cancer [see Warnings and precautions (5.2)].
- Estrogen-dependent neoplasia [see Warnings and Precautions (5.2)].
- Active DVT, PE, or history of these conditions [see Warnings and Precautions (5.1)].
- Active arterial thromboembolic disease (for example, stroke and MI) or a history of these conditions [see warnings and Precautions (5.1)].
- Known anaphylactic reaction, or angioedema, or hypersensitivity to ELESTRIN.
- Hepatic impairment or disease.
- Protein C, protein S, or antithrombin deficiency, or other known thrombophilic disorders.

5 WARNINGS AND PRECAUTIONS

5.1 Cardiovascular Disorders

Increased risk of stroke and DVT are reported with estrogen-alone therapy.

Increased risk of PE, DVT, stroke and MI are reported with estrogen plus progestin therapy. Immediately discontinue estrogen with or without progestin therapy if any of these occur or is suspected.

Manage appropriately any risk factors for arterial vascular disease (for example, hypertension, diabetes mellitus, tobacco use, hypercholesterolemia, and obesity) and/or venous thromboembolism (VTE) (for example, personal history or family history of VTE, obesity, and systemic lupus erythematosus).

Stroke

The WHI estrogen-alone substudy reported a statistically significant increased risk of stroke in women 50 to 79 years of age receiving daily CE (0.625 mg)-alone compared to women in the same age group receiving placebo (45 versus 33 strokes per 10,000 women-years, respectively). The increase in risk was demonstrated in year 1 and persisted [see Clinical Studies (14.2)]. Immediately discontinue estrogen-alone therapy if a stroke occurs or is suspected.

Subgroup analyses of women 50 to 59 years of age suggest no increased risk of stroke for those women receiving CE (0.625 mg)-alone versus those receiving placebo (18 versus 21 per 10,000 women-years).^1

The WHI estrogen plus progestin substudy reported a statistically significant increased risk of stroke in women 50 to 79 years of age receiving daily CE (0.625 mg) plus MPA (2.5 mg) compared to women in the same age group receiving placebo (33 versus 25 strokes per 10,000 women-years) [see Clinical Studies (14.2)]. The increase in risk was demonstrated after the first year and persisted.^1 Immediately discontinue estrogen plus progestin therapy if a stroke occurs or is suspected.

Coronary Heart Disease

The WHI estrogen-alone substudy reported no overall effect on coronary heart disease (CHD) events (defined as nonfatal MI, silent MI and CHD death) in women receiving estrogen-alone compared to placebo^2 [see Clinical Studies (14.2)].

Subgroup analyses of women 50 to 59 years of age, who were less than 10 years since menopause, suggest a reduction (not statistically significant) in CHD events in those women receiving daily CE (0.625 mg)-alone compared to placebo (8 versus 16 per 10,000 women-years).^1

The WHI estrogen plus progestin substudy reported an increased risk of CHD events (not statistically significant) in women receiving daily CE (0.625 mg) plus MPA (2.5 mg) compared to women receiving placebo (41 versus 34 per 10,000 women-years)^1. An increase in relative risk was demonstrated in year 1, and a trend toward decreasing relative risk was reported in years 2 through 5 [see Clinical Studies (14.2)].

In postmenopausal women with documented heart disease (n = 2,763, average 66.7 years of age), in a controlled clinical trial of secondary prevention of cardiovascular disease (Heart and Estrogen/Progestin Replacement Study; HERS) treatment with daily CE (0.625 mg) plus MPA (2.5 mg) demonstrated no cardiovascular benefit. During an average follow-up of 4.1 years, treatment with CE plus MPA did not reduce the overall rate of CHD events in postmenopausal women with established coronary heart disease. There were more CHD events in the CE plus MPA-treated group than in the placebo group in year 1, but not during the subsequent years. Two thousand, three hundred and twenty-one (2,321) women from the original HERS trial agreed to participate in an open label extension of HERS, HERS II. Average follow-up in HERS II was an additional 2.7 years, for a total of 6.8 years overall. Rates of CHD events were comparable among women in the CE plus MPA group and the placebo group in HERS, HERS II, and overall.

Venous Thromboembolism

In the WHI estrogen-alone substudy, the risk of VTE (DVT and PE) was increased for women receiving daily CE (0.625 mg)-alone compared to placebo (30 versus 22 per 10,000 women-years), although only the increased risk of DVT reached statistical significance (23 versus 15 per 10,000 women-years). The increase in VTE risk was demonstrated during the first 2 years^3 [see Clinical Studies (14.2)]. Immediately discontinue estrogen-alone therapy if a VTE occurs or is suspected.

The WHI estrogen plus progestin substudy reported a statistically significant 2-fold greater rate of VTE in women receiving daily CE (0.625 mg) plus MPA (2.5 mg) compared to women receiving placebo (35 versus 17 per 10,000 women-years). Statistically significant increases in risk for both DVT (26 versus 13 per 10,000 women-years) and PE (18 versus 8 per 10,000 women-years) were also demonstrated. The increase in VTE risk was demonstrated during the first year and persisted^4 [see Clinical Studies (14)]. Immediately discontinue estrogen plus progestin therapy if a VTE occurs or is suspected.

If feasible, discontinue estrogens at least 4 to 6 weeks before surgery of the type associated with an increased risk of thromboembolism, or during periods of prolonged immobilization.

5.2 Malignant Neoplasms

Endometrial Cancer

An increased risk of endometrial cancer has been reported with the use of unopposed estrogen therapy in a woman with a uterus. The reported endometrial cancer risk among unopposed estrogen users is about 2 to 12 times greater than in non-users and appears dependent on duration of treatment and on estrogen dose. Most studies show no significant increased risk associated with use of estrogens for less than 1 year. The greatest risk appears associated with prolonged use, with an increased risk of 15 to 24-fold for 5 to 10 years or more. This risk has been shown to persist for at least 8 to 15 years after estrogen therapy is discontinued.

Clinical surveillance of all women using estrogen-alone or estrogen/progestin combinations is important. Perform adequate diagnostic measures, including directed or random endometrial sampling when indicated, to rule out malignancy in postmenopausal women with persistent or recurring abnormal vaginal bleeding with unknown etiology.

There is no evidence that the use of natural estrogens results in a different endometrial risk profile than synthetic estrogens of equivalent estrogen dose. Adding a progestin to estrogen therapy has been shown to reduce the risk of endometrial hyperplasia, which may be a precursor to endometrial cancer.

In a 12-week clinical trial, one case of complex hyperplasia with atypia was reported in the ELESTRIN 1.7 g per day dose.

Breast Cancer

The WHI substudy of daily CE (0.625 mg)-alone provided information about breast cancer in estrogen-alone users. In the WHI estrogen-alone substudy, after an average of follow-up of 7.1 years, daily CE-alone was not associated with an increased risk of invasive breast cancer [relative risk (RR) 0.80] compared to placebo^5 [see Clinical Studies (14.2)].

After a mean follow-up of 5.6 years, the WHI substudy of daily CE (0.625 mg) plus MPA (2.5 mg) reported an increased risk of invasive breast cancer in women who took daily CE plus MPA compared to placebo.

In this substudy, prior use of estrogen-alone or estrogen plus progestin therapy was reported by 26 percent of the women. The relative risk of invasive breast cancer was 1.24, and the absolute risk was 41 versus 33 cases per 10,000 women-years, for CE plus MPA compared with placebo. Among women who reported prior use of hormone therapy, the relative risk of invasive breast cancer was 1.86, and the absolute risk was 46 versus 25 cases per 10,000 women-years, for CE plus MPA compared with placebo. Among women who reported no prior use of hormone therapy, the relative risk of invasive breast cancer was 1.09, and the absolute risk was 40 versus 36 cases per 10,000 women-years, for CE plus MPA compared with placebo. In the same substudy, invasive breast cancers were larger, were more likely to be node positive, and were diagnosed at a more advanced stage in the CE (0.625 mg) plus MPA (2.5 mg) group compared with the placebo group. Metastatic disease was rare with no apparent difference between the two groups. Other prognostic factors such as histologic subtype, grade and hormone receptor status did not differ between the groups.^6 [see Clinical Studies (14.2)].

Consistent with the WHI clinical trial, observational studies have also reported an increased risk of breast cancer with estrogen plus progestin therapy, and a smaller increase in the risk for breast cancer with estrogen-alone therapy, after several years of use. One large meta-analysis of prospective cohort studies reported increased risks that were dependent upon duration of use and could last up to > 10 years after discontinuation of estrogen plus progestin therapy and estrogen-alone therapy. Extension of WHI trials also demonstrated increased breast cancer risk associated with estrogen plus progestin therapy. Observational studies also suggest that the risk of breast cancer was greater, and became apparent earlier, with estrogen plus progestin therapy as compared to estrogen-alone therapy. These studies have not generally found significant variation in the risk of breast cancer among different estrogen plus progestin combinations, doses, or routes of administration.

The use of estrogen-alone and estrogen plus progestin has been reported to result in an increase in abnormal mammograms requiring further evaluation.

All women should receive yearly breast examinations by a healthcare provider and perform monthly self-examinations. In addition, mammography examinations should be scheduled based on patient age, risk factors, and prior mammogram results.

Ovarian Cancer

The CE plus MPA substudy of WHI reported that estrogen plus progestin increased the risk of ovarian cancer. After an average follow-up of 5.6 years, the relative risk for ovarian cancer for CE plus MPA versus placebo was 1.58 [95 percent CI, 0.77-3.24] but it was not statistically significant. The absolute risk for CE plus MPA versus placebo was 4 versus 3 cases per 10,000 women-years.^7

A meta-analysis of 17 prospective and 35 retrospective epidemiology studies found that women who used hormonal therapy for menopausal symptoms had an increased risk for ovarian cancer. The primary analysis, using case-control comparisons, included 12,110 cancer cases from the 17 prospective studies. The relative risks associated with current use of hormonal therapy was 1.41 (95% confidence interval [CI] 1.32-1.50); there was no difference in the risk estimates by duration of the exposure (less than 5 years [median of 3 years] vs. greater than 5 years [median of 10 years] of use before the cancer diagnosis). The relative risk associated with combined current and recent use (discontinued use within 5 years before cancer diagnosis) was 1.37 (95% CI 1.27-1.48), and the elevated risk was significant for both estrogen-alone and estrogen plus progestin products. The exact duration of hormone therapy use associated with an increased risk of ovarian cancer, however, is unknown.

5.3 Probable Dementia

In the WHI Memory Study (WHIMS) estrogen-alone ancillary study, a population of 2,947 hysterectomized women 65 to 79 years of age was randomized to daily CE (0.625 mg)-alone or placebo.

After an average follow-up of 5.2 years, 28 women in the estrogen-alone group and 19 women in the placebo group were diagnosed with probable dementia. The relative risk of probable dementia for CE-alone versus placebo was 1.49 (95 percent CI, 0.83-2.66). The absolute risk of probable dementia for CE-alone versus placebo was 37 versus 25 cases per 10,000 women-years^8 [see Use in Specific Populations (8.5), and Clinical Studies (14.3)].

In the WHIMS estrogen plus progestin ancillary study, a population of 4,532 postmenopausal women 65 to 79 years of age was randomized to daily CE (0.625 mg) plus MPA (2.5 mg) or placebo.

After an average follow-up of 4 years, 40 women in the CE plus MPA group and 21 women in the placebo group were diagnosed with probable dementia. The relative risk of probable dementia for CE plus MPA versus placebo was 2.05 (95% CI, 1.21-3.48). The absolute risk of probable dementia for CE plus MPA versus placebo was 45 versus 22 cases per 10,000 women-years^8 [see Use in Specific Populations (8.5), and Clinical Studies (14.3)].

When data from the two populations in the WHIMS estrogen-alone and estrogen plus progestin ancillary studies were pooled as planned in the WHIMS protocol, the reported overall relative risk for probable dementia was 1.76 (95% CI, 1.19-2.60). Since both ancillary studies were conducted in women 65 to 79 years of age, it is unknown whether these findings apply to younger postmenopausal women^8 [see Use in Specific Populations (8.5), and Clinical Studies (14.3)].

5.4 Gallbladder Disease

A 2- to 4-fold increase in the risk of gallbladder disease requiring surgery in postmenopausal women receiving estrogens has been reported.

5.5 Hypercalcemia

Estrogen administration may lead to severe hypercalcemia in women with breast cancer and bone metastases. Discontinue estrogens, including ELESTRIN if hypercalcemia occurs, and take appropriate measures to reduce the serum calcium level.

5.6 Visual Abnormalities

Retinal vascular thrombosis has been reported in women receiving estrogens. Discontinue ELESTRIN pending examination if there is sudden partial or complete loss of vision, or a sudden onset of proptosis, diplopia, or migraine. Discontinue estrogens, including ELESTRIN, if examination reveals papilledema or retinal vascular lesions.

5.7 Addition of a Progestin When a Woman Has Not Had a Hysterectomy

Studies of the addition of a progestin for 10 or more days of a cycle of estrogen administration, or daily with estrogen in a continuous regimen, have reported a lowered incidence of endometrial hyperplasia than would be induced by estrogen treatment alone. Endometrial hyperplasia may be a precursor to endometrial cancer.

There are, however, possible risks that may be associated with the use of progestins with estrogens compared to estrogen-alone regimens. These include an increased risk of breast cancer.

5.8 Elevated Blood Pressure

In a small number of case reports, substantial increases in blood pressure have been attributed to idiosyncratic reactions to estrogens. In a large, randomized, placebo-controlled clinical trial, a generalized effect of estrogens on blood pressure was not seen.

5.9 Exacerbation of Hypertriglyceridemia

In women with pre-existing hypertriglyceridemia, estrogen therapy may be associated with elevations of plasma triglycerides leading to pancreatitis. Consider discontinuation of ELESTRIN if pancreatitis occurs.

5.10 Hepatic Impairment and/or Past History of Cholestatic Jaundice

Estrogens may be poorly metabolized in women with hepatic impairment. Exercise caution in any woman with a history of cholestatic jaundice associated with past estrogen use or with pregnancy. In the case of recurrence of cholestatic jaundice, discontinued ELESTRIN.

5.11 Exacerbation of Hypothyroidism

Estrogen administration leads to increased thyroid-binding globulin (TBG) levels. Women with normal thyroid function can compensate for the increased TBG by making more thyroid hormone, thus maintaining free T4 and T3 serum concentrations in the normal range. Women dependent on thyroid hormone replacement therapy who are also receiving estrogens may require increased doses of their thyroid replacement therapy. Monitor thyroid function in these women during treatment with ELESTRIN to maintain their free thyroid hormone levels in an acceptable range.

5.12 Fluid Retention

Estrogens may cause some degree of fluid retention. Monitor any woman with a condition(s) that might predispose her to fluid retention, such as cardiac or renal impairment. Discontinue estrogen-alone therapy, including ELESTRIN, with evidence of medically concerning fluid retention.

5.13 Hypocalcemia

Estrogen-induced hypocalcemia may occur in women with hypoparathyroidism. Consider whether the benefits of estrogen therapy, including ELESTRIN, outweigh the risks in such women.

5.14 Exacerbation of Endometriosis

A few cases of malignant transformation of residual endometrial implants have been reported in women treated post-hysterectomy with estrogen-alone therapy. Consider the addition of a progestin for women known to have residual endometriosis post-hysterectomy.

5.15 Hereditary Angioedema

Exogenous estrogens may exacerbate symptoms of angioedema in women with hereditary angioedema. Consider whether the benefits of estrogen therapy outweigh the risks in such women.

5.16 Exacerbation of Other Conditions

Estrogen therapy, including ELESTRIN, may cause an exacerbation of asthma, diabetes mellitus, epilepsy, migraine, porphyria, systemic lupus erythematosus, and hepatic hemangiomas. Consider whether the benefits of estrogen therapy outweigh the risks in such women.

5.17 Photosensitivity or Photoallergy

Increased sensitivity to direct exposure to the sun on areas of ELESTRIN application has not been evaluated.

5.18 Sunscreen Application

Estradiol absorption was increased when sunscreen was applied 10 minutes before ELESTRIN application. Do not apply sunscreen to the application site of ELESTRIN until at least 25 minutes after the application of ELESTRIN.

Concomitant application of sunscreen and ELESTRIN to the same application site for 7 or more days may increase estradiol absorption. Avoid applying sunscreen to the area of ELESTRIN application for an extended period of 7 or more days [see Clinical Pharmacology, Pharmacokinetics (12.3)].

5.19 Miscellaneous

Alcohol based gels, including ELESTRIN, are potentially flammable. Avoid fire, flame, or smoking until ELESTRIN has dried.

5.20 Laboratory Tests

Serum follicle stimulating hormone (FSH) and estradiol levels have not been shown to be useful in the management of moderate to severe vasomotor symptoms.

5.21 Drug-Laboratory Test Interactions

- Accelerated prothrombin time, partial thromboplastin time, and platelet aggregation time; increased platelet count; increased factors II, VII antigen, VIII antigen, VIII coagulant activity, IX, X, XII, VII-X complex, II-VII-X complex, and beta-thromboglobulin; decreased levels of anti-factor Xa and antithrombin III, decreased antithrombin III activity; increased levels of fibrinogen and fibrinogen activity; increased plasminogen antigen and activity.
- Increased thyroid binding globulin (TBG) levels leading to increased circulating total thyroid hormone levels as measured by protein-bound iodine (PBI), T4 levels (by column or by radioimmunoassay) or T3 levels by radioimmunoassay. T3 resin uptake is decreased, reflecting the elevated TBG. Free T4 and free T3 concentrations are unaltered. Women on thyroid replacement therapy may require higher doses of thyroid hormone.
- Other binding proteins may be elevated in serum, for example, corticosteroid binding globulin (CBG), sex hormone-binding globulin (SHBG), leading to increased total circulating corticosteroids and sex steroids, respectively. Free hormone concentrations, such as testosterone and estradiol, may be decreased. Other plasma proteins may be increased (angiotensinogen/renin substrate, alpha-1-antitrypsin, ceruloplasmin).
- Increased plasma high-density lipoprotein (HDL) and HDL2 cholesterol subfraction concentrations, reduced low-density lipoprotein (LDL) cholesterol concentration, and increased triglycerides levels.
- Impaired glucose tolerance.

6 ADVERSE REACTIONS

The following serious adverse reactions are discussed elsewhere in the labeling:

- Cardiovascular Disorders [see Boxed Warning, and Warnings and Precautions (5.1)].
- Malignant Neoplasms [see Boxed Warning, and Warnings and Precautions (5.2)].

6.1 Clinical Trials Experience

Because clinical trials are conducted under widely varying conditions, adverse reaction rates observed in the clinical trials of a drug cannot be directly compared to rates in the clinical trials of another drug and may not reflect the rates observed in practice.

ELESTRIN was studied in a placebo-controlled trial that included a total of 484 postmenopausal women. The adverse reactions that occurred at a rate greater than 5 percent in any of the treatment groups are summarized in Table 1.

TABLE 1 - Incidence of Treatment-Emergent Adverse Reactions Occurring in ≥ 5 Percent of Women
Body System / Signs and Symptoms | Number (%) of Women
Body System / Signs and Symptoms | Placebo (n = 137) | ELESTRIN 0.87 g/day (n = 136) | ELESTRIN 1.7 g/day (n = 142)
Reproductive system & breast disorders
Breast tenderness | 5 (3.6) | 9 (6.6) | 11 (7.7)
Metrorrhagia | 3 (2.2) | 6 (4.4) | 13 (9.2)
Respiratory, thoracic & mediastinal disorders
Nasopharyngitis | 10 (7.3) | 14 (10.3) | 12 (8.5)
Upper respiratory tract infection | 5 (3.6) | 8 (5.9) | 5 (3.5)

6.2 Postmarketing Experience

The following adverse reactions have been identified during post-approval use of ELESTRIN. Because these reactions are reported voluntarily from a population of uncertain size, it is not always possible to reliably estimate their frequency or establish a causal relationship to drug exposure.

Genitourinary System

Changes in vaginal bleeding pattern and abnormal withdrawal bleeding or flow; breakthrough bleeding; spotting; dysmenorrhea; increase in size of uterine leiomyomata; vaginitis, including vaginal candidiasis; change in amount of cervical secretion; changes in cervical ectropion; ovarian cancer; endometrial hyperplasia; endometrial cancer.

Breasts

Tenderness; enlargement, pain, nipple discharge, galactorrhea; fibrocystic breast changes; breast cancer.

Cardiovascular

Deep and superficial venous thrombosis; pulmonary embolism; thrombophlebitis; myocardial infarction; stroke; increase in blood pressure.

Gastrointestinal

Nausea, vomiting; abdominal cramps, bloating; cholestatic jaundice; increased incidence of gallbladder disease; pancreatitis, enlargement of hepatic hemangiomas.

Skin

Chloasma or melasma that may persist when drug is discontinued; erythema multiforme; erythema nodosum; hemorrhagic eruption; loss of scalp hair; hirsutism; pruritus, rash.

Eyes

Retinal vascular thrombosis, intolerance to contact lenses.

Central Nervous System

Headache; migraine; dizziness; mental depression; chorea; nervousness; mood disturbances; irritability; exacerbation of epilepsy, dementia.

Miscellaneous

Increase or decrease in weight; reduced carbohydrate tolerance; aggravation of porphyria; edema; arthralgias; leg cramps; changes in libido; urticaria, angioedema, anaphylactoid/anaphylactic reactions; hypocalcemia; exacerbation of asthma; increased triglycerides.

7 DRUG INTERACTIONS

In vitro and in vivo studies have shown that estrogens are metabolized partially by cytochrome P450 3A4 (CYP3A4). Therefore, inducers or inhibitors of CYP3A4 may affect estrogen drug metabolism. Inducers of CYP3A4, such as St. John’s wort (Hypericum perforatum) preparations, phenobarbital, carbamazepine, and rifampin, may reduce plasma concentrations of estrogens, possibly resulting in a decrease in therapeutic effects and/or changes in the uterine bleeding profile. Inhibitors of CYP3A4, such as erythromycin, clarithromycin, ketoconazole, itraconazole, ritonavir, and grapefruit juice, may increase plasma concentrations of estrogens and result in adverse reactions.

8 USE IN SPECIFIC POPULATIONS

8.1 Pregnancy

Risk Summary

ELESTRIN is not indicated for use in pregnancy. There are no data with the use of ELESTRIN in pregnant women; however, epidemiologic studies and meta-analyses have not found an increased risk of genital or nongenital birth defects (including cardiac anomalies or limb-reduction defects) following exposure to combined hormonal contraceptives (estrogen and progestins) before conception or during early pregnancy. Animal studies to evaluate embryo/fetal toxicity were not conducted with ELESTRIN.

8.2 Lactation

Risk Summary

Estrogens are present in human milk and can reduce milk production in breast-feeding women. This reduction can occur at any time but is less likely to occur once breast-feeding is well-established. The developmental and health benefits of breast-feeding should be considered along with the mother’s clinical need for ELESTRIN and any potential adverse effects on the breast-fed child from ELESTRIN or from the underlying maternal condition.

8.4 Pediatric Use

ELESTRIN is not indicated in pediatric patients. Clinical studies have not been conducted in the pediatric population.

8.5 Geriatric Use

There have not been sufficient numbers of geriatric women involved in clinical studies utilizing ELESTRIN to determine whether those over 65 years of age differ from younger subjects in their response to ELESTRIN.

The Women’s Health Initiative Study

In the WHI estrogen-alone substudy (daily CE [0.625 mg]-alone versus placebo), there was a higher relative risk of stroke in women greater than 65 years of age [see Clinical Studies (14.2)].

In the WHI estrogen plus progestin substudy (daily CE [0.625 mg] plus MPA [2.5 mg] versus placebo), there was a higher relative risk of nonfatal stroke and invasive breast cancer in women greater than 65 years of age [see Clinical Studies (14.2)].

The Women’s Health Initiative Memory Study

In the WHIMS ancillary studies of postmenopausal women 65 to 79 years of age, there was an increased risk of developing probable dementia in women receiving estrogen-alone or estrogen plus progestin when compared to placebo [see Warnings and Precautions (5.3), and Clinical Studies (14.3)].

Since both ancillary studies were conducted in women 65 to 79 years of age, it is unknown whether these findings apply to younger postmenopausal women^8 [see Warnings and Precautions (5.3), and Clinical Studies (14.3)].

10 OVERDOSAGE

Overdosage of estrogen may cause nausea, vomiting, breast tenderness, abdominal pain, drowsiness and fatigue, and withdrawal bleeding may occur in women. Treatment of overdose consists of discontinuation of ELESTRIN therapy with institution of appropriate symptomatic care.

11 DESCRIPTION

ELESTRIN (estradiol gel) contains 0.06% of estradiol, in a colorless, non-staining hydroalcoholic gel base. One pump actuation delivers ELESTRIN in a unit dose of 0.52 mg of estradiol in 0.87 g of gel.

Estradiol is a white crystalline powder, chemically described as estra-1,3,5(10)-triene-3,17-diol, (17β)-. It has a molecular formula of C18H24O2•½H2O and molecular weight of 281.4.

The structural formula is:

The active component of ELESTRIN is estradiol. The remaining components of the gel (ethanol, propylene glycol, diethylene glycol monoethyl ether, carbomer homopolymer type C, triethanolamine, edetate disodium, and purified water) are pharmacologically inactive.

12 CLINICAL PHARMACOLOGY

12.1 Mechanism of Action

Endogenous estrogens are largely responsible for the development and maintenance of the female reproductive system and secondary sexual characteristics. Although circulating estrogens exist in a dynamic equilibrium of metabolic interconversions, estradiol is the principal intracellular human estrogen and is substantially more potent than its metabolites, estrone and estriol, at the receptor level.

The primary source of estrogen in normally cycling adult women is the ovarian follicle, which secretes 70 to 500 mcg of estradiol daily, depending on the phase of the menstrual cycle. After menopause, most endogenous estrogen is produced by conversion of androstenedione, secreted by the adrenal cortex, to estrone in the peripheral tissues. Thus, estrone and the sulfate-conjugated form, estrone sulfate, are the most abundant circulating estrogens in postmenopausal women.

Estrogens act through binding to nuclear receptors in estrogen-responsive tissues. To date, two estrogen receptors have been identified. These vary in proportion from tissue to tissue.

Circulating estrogens modulate the pituitary secretion of the gonadotropins, luteinizing hormone (LH) and FSH through a negative feedback mechanism. Estrogens act to reduce the elevated levels of these hormones seen in postmenopausal women.

12.2 Pharmacodynamics

Generally, a serum estrogen concentration does not predict an individual woman’s therapeutic response to ELESTRIN nor her risk for adverse outcomes. Likewise, exposure comparisons across different estrogen products to infer efficacy or safety for the individual woman may not be valid.

12.3 Pharmacokinetics

Absorption

Steady-state serum concentrations of estradiol are achieved in approximately 3 days following daily application of ELESTRIN to the upper arm.

Pharmacokinetic parameters for estradiol on Day 14 following daily application of 0.87 g or 1.7 g of ELESTRIN are summarized in Table 2. Dose dependent PK parameters for ELESTRIN 0.87 g and 1.7 g indicated the dose and serum estradiol (E2) concentrations to be linearly related but not dose-proportional (i.e., doubling in dose led to a 2.5- to 3.0-fold increase in PK parameters). The nominal mean delivery rates of estradiol using the baseline-adjusted average serum concentrations from pharmacokinetic studies using 0.87 g per day and 1.7 g per day are 0.0125 mg per day and 0.0375 mg per day, respectively.

TABLE 2 - Summary of Unadjusted PK Parameters for Estradiol after 14 Days of Dosing
Pharmacokinetic Parameter | 0.87 g ELESTRIN (0.52 mg/d Estradiol) Mean | 1.7 g ELESTRIN (1.04 mg/d Estradiol) Mean
AUC0-24 (pg’hr/mL) | 335.2 | 940.2
Cmax (pg/mL) | 21.6 | 66.7
Cave (pg/mL) | 15.4 | 39.2
Cmin (pg/mL) | 9.4 | 21.1
Tmax (h) [Tmax shown as median (range)] | 18 (1 - 20) | 4 (1 - 20)
Fluctuation Index | 0.80 | 1.16
E2:E1 [E2:E1 (estradiol:estrone) ratio] ratio | 0.53 | 0.98

Mean concentrations of estradiol over a 24-hour period on Day 14 are shown in Figure 1.

Based on the Cave values at steady state, the E2:E1 ratio was 0.53 for the 0.87 g and 0.98 for the 1.7 g doses. The significance of this finding is that the 1.7 g dose produced an E2:E1 ratio of a premenopausal woman. The 1.7 g dose of ELESTRIN reached the goal of restoring the E2:E1 ratio (~1.0) to that observed in premenopausal women in the early follicular phase of the menstrual cycle.

Application of sunscreen 10 minutes before application of ELESTRIN increased the exposure to estradiol by approximately 55 percent. No significant change in estradiol exposure was observed when sunscreen was applied 25 minutes after application of ELESTRIN. In the same study, prolonged (7 days) concomitant application of sunscreen to the site of ELESTRIN application increased exposure to estradiol by about 2-fold, regardless of whether it was applied before or after application of ELESTRIN.

Distribution

The distribution of exogenous estrogens is similar to that of endogenous estrogens. Estrogens are widely distributed in the body and are generally found in higher concentrations in the sex hormone target organs. Estrogens circulate in blood largely bound to SHBG and albumin.

Metabolism

Exogenous estrogens are metabolized in the same manner as endogenous estrogens. Circulating estrogens exist in a dynamic equilibrium of metabolic interconversions. These transformations take place mainly in the liver. Estradiol is converted reversibly to estrone, and both can be converted to estriol, which is a major urinary metabolite. Estrogens also undergo enterohepatic recirculation via sulfate and glucuronide conjugation in the liver, biliary secretion of conjugates into the intestine, and hydrolysis in the intestine followed by reabsorption.

In postmenopausal women, a significant proportion of the circulating estrogens exist as sulfate conjugates, especially estrone sulfate, which serves as a circulating reservoir for the formation of more active estrogens.

Excretion

Estradiol, estrone and estriol are excreted in the urine along with glucuronide and sulfate conjugates.

Potential for Estradiol Transfer

The potential for estradiol transfer between treated postmenopausal female subjects and their untreated male partners was evaluated. Two and 8 hours after women applied 2.6 g ELESTRIN to one arm (12 women per time point), they engaged in direct arm-to-arm contact with a male partner for 5 minutes. No significant changes in estradiol pharmacokinetic parameters were observed in the male partners after contact.

Less than 10 percent of the estradiol dose was measured on the skin at 2 and 8 hours after application. After washing the application site with soap and water at 8 hours after application, about 1 percent of the dose of estradiol was measurable.

13 NONCLINICAL TOXICOLOGY

13.1 Carcinogenesis, Mutagenesis, Impairment of Fertility

Long-term continuous administration of natural and synthetic estrogens in certain animal species increases the frequency of carcinomas of the breast, uterus, cervix, vagina, testis, and liver.

14 CLINICAL STUDIES

14.1 Effects on Vasomotor Symptoms in Postmenopausal Women

A randomized, double-blind, placebo-controlled clinical trial evaluated the efficacy of 12-week treatment with three different daily doses of ELESTRIN for the treatment of vasomotor symptoms in 484 postmenopausal women between 28 and 74 years of age (mean 54 years; 83-88 percent Caucasian per group) who had at least 60 moderate-to-severe hot flushes per week at baseline. At baseline, mean hot flushes is 13 per day, mean serum estradiol is 11.2-13.2 pg/mL, and prior hormone/estrogen therapy is 75.7-84.5 percent. Participants applied placebo, 1.7 g (1.04 mg estradiol), or 2.6 g (1.56 mg estradiol) once daily to the upper arm. The study was amended to identify the lowest effective dose of ELESTRIN and limit the number of women exposed to the 2.6 g dose. After the study amendment, ELESTRIN 0.87 g (0.52 mg estradiol) was added and the 2.6 g was discontinued from further enrollment. Reduction in both the frequency and severity of moderate to severe hot flushes was statistically significant for the ELESTRIN 1.7 g per day dose compared to placebo at week 4. Statistically significant reductions in both the frequency and severity of moderate to severe hot flushes when compared to placebo were delayed for the ELESTRIN 0.87 g per day dose to week 5. Both the 0.87 g per day and 1.7 g per day doses were statistically significant compared to placebo at week 12. Statistically significant reductions in the frequency and severity of daily moderate-to-severe hot flush rate compared to placebo were noted beginning at week 3 for the 1.7 g per day ELESTRIN treatment (data on file). The reductions in frequency and severity are shown in Table 3.

TABLE 3 - Mean Change from Baseline [Differences from baseline based on LS means derived from the ANCOVA model with factors for baseline, treatment, site, and treatment-by-baseline interaction.] in the Number and Severity of Hot Flushes after ELESTRIN Treatment
Evaluation |  | Placebo (N=137) | ELESTRIN 0.87 g/day (N=136) | ELESTRIN 1.7 g/day (N=142)
Number of Daily Hot Flushes
Baseline (Mean ± SD) [Unadjusted means and standard deviations based on the first 14 days of the Screening Period.] |  | 13.5 ± 4.5 | 13.3 ± 4.6 | 13.1 ± 6.5
Mean Change: | Week 4 | -5.1 | -6.5 [P=ns] | -8.0 [P<0.0001 for treatment comparison with placebo (Dunnett’s test).]
Week 5 |  | -5.1 | -7.5 [P<0.01 P<0.001] | -8.8
Week 12 |  | -5.4 | -8.5 | -10.0
Daily Hot Flush Severity [Severity score: 1=mild, 2=moderate, 3=severe.]
Baseline (Mean ± SD) |  | 2.4 ± 0.3 | 2.4 ± 0.3 | 2.4 ± 0.3
Mean Change: | Week 4 | -0.2 | -0.5 | -0.7
Week 5 |  | -0.2 | -0.5 | -0.8
Week 12 |  | -0.3 | -0.8 | -1.2
SD: standard deviation

14.2 Women’s Health Initiative Studies

The WHI enrolled approximately 27,000 predominantly healthy postmenopausal women in two substudies to assess the risks and benefits of daily oral CE (0.625 mg)-alone or in combination with MPA (2.5 mg) compared to placebo in the prevention of certain chronic diseases. The primary endpoint was the incidence of CHD (defined as nonfatal MI, silent MI and CHD death), with invasive breast cancer as the primary adverse outcome. A “global index” included the earliest occurrence of CHD, invasive breast cancer, stroke, PE, endometrial cancer (only in the CE plus MPA substudy), colorectal cancer, hip fracture, or death due to other cause. These substudies did not evaluate the effects of CE-alone or CE plus MPA on menopausal symptoms.

WHI Estrogen-Alone Substudy

The WHI estrogen-alone substudy was stopped early because an increased risk of stroke was observed, and it was deemed that no further information would be obtained regarding the risk and benefits of estrogen-alone in predetermined endpoints.

Results of the estrogen-alone substudy, which included 10,739 women (average 63 years of age, range 50 to 79; 75.3 percent White, 15.1 percent Black, 6.1 percent Hispanic, 3.6 percent Other), after an average follow-up of 7.1 years are presented in Table 4.

TABLE 4 - Relative and Absolute Risk Seen in the Estrogen-Alone substudy of WHI [Adapted from numerous WHI publications. WHI publications can be viewed at www.nhlbi.nih.gov/whi.]
Event | Relative Risk CE vs. Placebo (95% nCl [Nominal confidence intervals unadjusted for multiple looks and multiple comparisons.]) | CE n = 5,310 | Placebo n = 5,429
Event | Relative Risk CE vs. Placebo (95% nCl [Nominal confidence intervals unadjusted for multiple looks and multiple comparisons.]) | Absolute Risk per 10,000 Women-Years
CHD events [Results are based on centrally adjudicated data for an average follow-up of 7.1 years.] | 0.95 (0.78-1.16) | 54 | 57
Non-fatal MI | 0.91 (0.73-1.14) | 40 | 43
CHD death | 1.01 (0.71-1.43) | 16 | 16
All Stroke | 1.33 (1.15-1.68) | 45 | 33
Ischemic stroke | 1.55 (1.19-2.01) | 38 | 25
Deep vein thrombosis [Not included in “global index”.] | 1.47 (1.06-2.06) | 23 | 15
Pulmonary embolism | 1.37 (0.90-2.07) | 14 | 10
Invasive breast cancer | 0.80 (0.62-1.04) | 28 | 34
Colorectal cancer | 1.08 (0.75-1.55) | 17 | 16
Hip fracture | 0.65 (0.45-0.94) | 12 | 19
Vertebral fractures | 0.64 (0.44-0.93) | 11 | 18
Lower arm/wrist fractures | 0.58 (0.47-0.72) | 35 | 59
Total fractures | 0.71 (0.64-0.80) | 144 | 197
Death due to other causes [Results are based on an average follow-up of 6.8 years.] [All deaths, except from breast or colorectal cancer, definite or probable CHD, PE or cerebrovascular disease.] | 1.08 (0.88-1.32) | 53 | 50
Overall mortality, | 1.04 (0.88-1.22) | 79 | 75
Global index [A subset of the events was combined in a “global index”, defined as the earliest occurrence of CHD events, invasive breast cancer, stroke, pulmonary embolism, endometrial cancer, colorectal cancer, hip fracture, or death due to other causes.] | 1.02 (0.92-1.13) | 206 | 201

For those outcomes included in the WHI “global index,” that reached statistical significance, the absolute excess risks per 10,000 women-years in the group treated with CE-alone were 12 more strokes, while the absolute risk reduction per 10,000 women-years was 7 fewer hip fractures.^9 The absolute excess risk of events included in the “global index” was a non-significant 5 events per 10,000 women-years. There was no difference between the groups in terms of all-cause mortality.

No overall difference for primary CHD events (nonfatal MI, silent MI and CHD death) and invasive breast cancer incidence in women receiving CE-alone compared with placebo was reported in final centrally adjudicated results from the estrogen-alone substudy, after an average follow-up of 7.1 years.

Centrally adjudicated results for stroke events from the estrogen-alone substudy, after an average follow-up of 7.1 years, reported no significant difference in the distribution of stroke subtype and severity, including fatal strokes, in women receiving estrogen-alone compared to placebo. Estrogen-alone therapy increased the risk of ischemic stroke, and this excess risk was present in all subgroups of women examined.^10

Timing of initiation of estrogen-alone therapy relative to the start of menopause may affect the overall risk benefit profile. The WHI estrogen-alone substudy stratified by age showed in women 50 to 59 years of age a non-significant trend toward reduced risk for CHD [hazard ratio (HR) 0.63 (95 percent CI, 0.36-1.09)] and overall mortality [HR 0.71 (95 percent CI, 0.46–1.11)].

WHI Estrogen Plus Progestin Substudy

The WHI estrogen plus progestin substudy was stopped early. According to the predefined stopping rule, after an average follow-up of 5.6 years of treatment, the increased risk of invasive breast cancer and cardiovascular events exceeded the specified benefits included in the “global index.” The absolute excess risk of events included in the “global index” was 19 per 10,000 women-years.

For those outcomes included in the WHI “global index” that reached statistical significance after 5.6 years of follow-up, the absolute excess risks per 10,000 women-years in the group treated with CE plus MPA were 7 more CHD events, 8 more strokes, 10 more PEs, and 8 more invasive breast cancers, while the absolute risk reduction per 10,000 women-years were 6 fewer colorectal cancers and 5 fewer hip fractures.

Results of the CE plus MPA substudy, which included 16,608 women (average 63 years of age, range 50 to 79; 83.9 percent White, 6.8 percent Black, 5.4 percent Hispanic, 3.9 percent Other) are presented in Table 5. These results reflect centrally adjudicated data after an average follow-up of 5.6 years.

TABLE 5 - Relative and Absolute Risk Seen in the Estrogen Plus Progestin Substudy of WHI at an Average of 5.6 Years [Adapted from numerous WHI publications. WHI publications can be viewed at www.nhlbi.nih.gov/whi.] [Results are based on centrally adjudicated.]
Event | Relative Risk CE/MPA vs. Placebo (95% nCl [Nominal confidence intervals unadjusted for multiple looks and multiple comparisons.]) | CE/MPA n = 8,506 | Placebo n = 8,102
Event | Relative Risk CE/MPA vs. Placebo (95% nCl [Nominal confidence intervals unadjusted for multiple looks and multiple comparisons.]) | Absolute Risk per 10,000 Women-Years
CHD events | 1.23 (0.99-1.53) | 41 | 34
Non-fatal MI | 1.28 (1.00-1.63) | 31 | 25
CHD death | 1.10 (0.70-1.75) | 8 | 8
All Stroke | 1.31 (1.03-1.68) | 33 | 25
Ischemic stroke | 1.44 (1.09-1.90) | 26 | 18
Deep vein thrombosis [Not included in “global index”.] | 1.95 (1.43-2.67) | 26 | 13
Pulmonary embolism | 2.13 (1.45-3.11) | 18 | 8
Invasive breast cancer [Includes metastatic and non-metastatic breast cancer with the exception of in situ breast cancer.] | 1.24 (1.01-1.54) | 41 | 33
Colorectal cancer | 0.61 (0.42-0.87) | 10 | 16
Endometrial cancer | 0.81 (0.48-1.36) | 6 | 7
Cervical cancer | 1.44 (0.47-4.42) | 2 | 1
Hip fracture | 0.67 (0.47-0.96) | 11 | 16
Vertebral fractures | 0.65 (0.46-0.92) | 11 | 17
Lower arm/wrist fractures | 0.71 (0.59-0.85) | 44 | 62
Total fractures | 0.76 (0.69-0.83) | 152 | 199
Overall mortality [All deaths, except from breast or colorectal cancer, definite or probable CHD, PE or cerebrovascular disease.] | 1.00 (0.83-1.19) | 52 | 52
Global Index [A subset of the events was combined in a “global index”, defined as the earliest occurrence of CHD events, invasive breast cancer, stroke, pulmonary embolism, endometrial cancer, colorectal cancer, hip fracture, or death due to other causes.] | 1.13 (1.02-1.25) | 184 | 165

Timing of initiation of estrogen plus progestin therapy relative to the start of menopause may affect the overall risk benefit profile. The WHI estrogen plus progestin substudy stratified by age showed in women 50 to 59 years of age a non-significant trend toward reduced risk for overall mortality [HR 0.69 (95 percent CI, 0.44-1.07)].

14.3 Women’s Health Initiative Memory Study

The WHIMS estrogen-alone ancillary study of WHI enrolled 2,947 predominantly healthy hysterectomized postmenopausal women 65 to 79 years of age (45 percent were 65 to 69 years of age, 36 percent were 70 to 74 years of age, and 19 percent were 75 years of age and older) to evaluate the effects of daily CE (0.625 mg)-alone on the incidence of probable dementia (primary outcome) compared to placebo.

After an average follow-up of 5.2 years, the relative risk of probable dementia for CE-alone versus placebo was 1.49 (95 percent CI, 0.83-2.66). The absolute risk of probable dementia for CE-alone versus placebo was 37 versus 25 cases per 10,000 women-years. Probable dementia as defined in the study included Alzheimer’s disease (AD), vascular dementia (VaD) and mixed type (having features of both AD and VaD). The most common classification of probable dementia in the treatment group and the placebo group was AD. Since the ancillary study was conducted in women 65 to 79 years of age, it is unknown whether these findings apply to younger postmenopausal women [see Warnings and Precautions (5.3) and Use in Specific Populations (8.5)].

The WHIMS estrogen plus progestin ancillary study enrolled 4,532 predominantly healthy postmenopausal women 65 years of age and older (47 percent were 65 to 69 years of age, 35 percent were 70 to 74 years of age, and 18 percent were 75 years of age and older) to evaluate the effects of daily CE (0.625 mg) plus MPA (2.5 mg) on the incidence of probable dementia (primary outcome) compared to placebo.

After an average follow-up of 4 years, the relative risk of probable dementia for CE plus MPA versus placebo was 2.05 (95 percent CI, 1.21-3.48). The absolute risk of probable dementia for CE plus MPA versus placebo was 45 versus 22 cases per 10,000 women-years. Probable dementia as defined in the study included AD, VaD and mixed types (having features of both AD and VaD). The most common classification of probable dementia in the treatment group and the placebo group was AD. Since the ancillary study was conducted in women 65 to 79 years of age, it is unknown whether these findings apply to younger postmenopausal women [see Warnings and Precautions (5.3) and Use in Specific Populations (8.5)].

When data from the two populations were pooled as planned in the WHIMS protocol, the reported overall relative risk for probable dementia was 1.76 (95 percent CI, 1.19-2.60). Differences between groups became apparent in the first year of treatment. It is unknown whether these findings apply to younger postmenopausal women [see Warnings and Precautions (5.3), and Use in Specific Populations (8.5)].

15 REFERENCES

1. Rossouw JE, et al. Postmenopausal Hormone Therapy and Risk of Cardiovascular Disease by Age and Years Since Menopause. JAMA. 2007;297:1465-1477.
2. Hsia J, et al. Conjugated Equine Estrogens and Coronary Heart Disease. Arch Int Med. 2006;166:357-365.
3. Curb JD, et al. Venous Thrombosis and Conjugated Equine Estrogen in Women Without a Uterus. Arch Int Med. 2006;166:772-780.
4. Cushman M, et al. Estrogen Plus Progestin and Risk of Venous Thrombosis. JAMA. 2004;292:1573-1580.
5. Stefanick ML, et al. Effects of Conjugated Equine Estrogens on Breast Cancer and Mammography Screening in Postmenopausal Women With Hysterectomy. JAMA. 2006;295:1647-1657.
6. Chlebowski RT, et al. Influence of Estrogen Plus Progestin on Breast Cancer and Mammography in Healthy Postmenopausal Women. JAMA. 2003;289:3234-3253.
7. Anderson GL, et al. Effects of Estrogen Plus Progestin on Gynecologic Cancers and Associated Diagnostic Procedures. JAMA. 2003;290:1739-1748.
8. Shumaker SA, et al. Conjugated Equine Estrogens and Incidence of Probable Dementia and Mild Cognitive Impairment in Postmenopausal Women. JAMA. 2004;291:2947-2958.
9. Jackson RD, et al. Effects of Conjugated Equine Estrogen on Risk of Fractures and BMD in Postmenopausal Women With Hysterectomy: Results From the Women’s Health Initiative Randomized Trial. J Bone Miner Res. 2006;21:817-828.
10. Hendrix SL, et al. Effects of Conjugated Equine Estrogen on Stroke in the Women’s Health Initiative. Circulation. 2006;113:2425-2434.

16 HOW SUPPLIED/STORAGE AND HANDLING

16.1 How Supplied

Elestrin (estradiol gel) 0.06% in a colorless, non-staining hydroalcoholic gel supplied in a non-aerosol, metered-dose pump container constructed of polypropylene. The drug product is contained within a collapsible inner liner/bag consisting of an inner and outer layer of low density polyethylene with a resealable polypropylene cap. Each pump container holds 35 g of gel and is capable of delivering 26 g of gel as 30 metered doses. Each metered dose delivers 0.87 g of gel which contains 0.52 mg of estradiol.

NDC 0037-4801-70.....Carton containing two ELESTRIN 35 g pump containers.

16.2 Storage and Handling

Store at 20° to 25°C (68° to 77°F); excursions permitted to 15° to 30°C (59° to 86°F). [See USP Controlled Room Temperature].

17 PATIENT COUNSELING INFORMATION

Advise women to read the FDA-approved patient labeling (Patient Information and Instructions for Use).

Vaginal Bleeding

Inform postmenopausal women to report any vaginal bleeding to their healthcare provider as soon as possible [see Warning and Precautions (5.2)].

Possible Serious Adverse Reactions with Estrogen-Alone Therapy

Inform postmenopausal women of possible serious adverse reactions of estrogen-alone therapy including Cardiovascular Disorders, Malignant Neoplasms, and Probable Dementia [see Warnings and Precautions (5.1, 5.2, 5.3)].

Possible Common Adverse Reactions with Estrogen-Alone Therapy

Inform postmenopausal women of possible less serious but common adverse reactions of estrogen-alone therapy such as headache, breast pain and tenderness, nausea and vomiting.

PATIENT INFORMATION

ELESTRIN® (el-LES-strin)
(estradiol gel)

Read this Patient Information before you start using ELESTRIN and each time you get a refill. There may be new information. This information does not take the place of talking to your healthcare provider about your medical condition or your treatment.

What is the most important information I should know about ELESTRIN (an estrogen hormone)?

- Using estrogen-alone increases your chance of getting cancer of the uterus (womb)Report any unusual vaginal bleeding right away while you are using ELESTRIN. Vaginal bleeding after menopause may be a warning sign of cancer of the uterus (womb). Your healthcare provider should check any unusual vaginal bleeding to find out the cause.
- Do not use estrogen-alone to prevent heart disease, heart attacks, strokes, or dementia (decline in brain function)
- Using estrogen-alone may increase your chances of getting strokes or blood clots
- Using estrogen-alone may increase your chance of getting dementia, based on a study of women age 65 years or older
- Do not use estrogens with progestins to prevent heart disease, heart attacks, strokes or dementia
- Using estrogens with progestins may increase your chances of getting heart attacks, strokes, breast cancer, or blood clots
- Using estrogens with progestins may increase your chance of getting dementia, based on a study of women age 65 years or older
- Only one estrogen-alone product and dose have been shown to increase your chances of getting strokes, blood clots, and dementia. Only one estrogen with progestin product and dose have been shown to increase your chances of getting heart attacks, strokes, breast cancer, blood clots, and dementia.
- Because other products and doses have not been studied in the same way, it is not known how the use of ELESTRIN will affect your chances of these conditions. You and your healthcare provider should talk regularly about whether you still need treatment with ELESTRIN.

What is ELESTRIN?

ELESTRIN is a prescription medicine in a colorless gel that contains the estrogen hormone estradiol. When applied to the skin, estradiol is absorbed through the skin into the blood stream.

What is ELESTRIN used for?

ELESTRIN is used after menopause to:

- Reduce moderate to severe hot flashes

Estrogens are hormones made by a woman’s ovaries. The ovaries normally stop making estrogens when a woman is between 45 to 55 years old. This drop in body estrogen levels causes the “change of life” or menopause (the end of monthly menstrual periods). Sometimes, both ovaries are removed during an operation before natural menopause takes place. The sudden drop in estrogen levels causes “surgical menopause.”

When estrogen levels begin dropping, some women develop very uncomfortable symptoms, such as feelings of warmth in the face, neck, and chest, or sudden intense feelings of heat and sweating (“hot flashes” or “hot flushes”). In some women, the symptoms are mild, and they will not need estrogens. In other women, symptoms can be more severe. You and your healthcare provider should talk regularly about whether you still need treatment with ELESTRIN.

Who should not use ELESTRIN?

Do not start ELESTRIN if you:

- have unusual vaginal bleeding
  Vaginal bleeding after menopause may be a warning sign of cancer of the uterus (womb). Your healthcare provider should check any unusual vaginal bleeding to find out the cause.
- have been diagnosed with a bleeding disorder
- currently have or have had certain cancers
  Estrogens may increase the chances of getting certain types of cancers, including cancer of the breast or uterus (womb). If you have or have had cancer, talk with your healthcare provider about whether you should use ELESTRIN.
- had a stroke or heart attack
- currently have or have had blood clots
- currently have or have had liver problems
- are allergic to ELESTRIN or any of its ingredients
See the list of ingredients in ELESTRIN at the end of this leaflet

Before you use ELESTRIN, tell your healthcare provider about all of your medical conditions, including if you:

- have any unusual vaginal bleeding
  Vaginal bleeding after menopause may be a warning sign of cancer of the uterus (womb). Your healthcare provider should check any unusual vaginal bleeding to find out the cause.
- have any other medical conditions that may become worse while you are using ELESTRIN
  Your healthcare provider may need to check you more carefully if you have certain conditions, such as asthma (wheezing), epilepsy (seizures), diabetes, migraine, endometriosis, lupus, angioedema (swelling of face and tongue), problems with your heart, liver, thyroid, kidneys, or have high calcium levels in your blood.
- are going to have surgery or will be on bed rest
  You may need to stop using ELESTRIN.
- are pregnant or think you may be pregnant
  ELESTRIN is not for pregnant women.
- are breastfeeding
  The hormone in ELESTRIN can pass into your breast milk.

Tell your healthcare provider about all the medicines you take, including prescription and over-the-counter medicines, vitamins, and herbal supplements. Some medicines may affect how ELESTRIN works. ELESTRIN may also affect how your other medicines work. Keep a list of your medicines and show it to your healthcare provider and pharmacist when you get new medicine.

How should I use ELESTRIN?

- Start at the lowest dose and talk to your healthcare provider about how well that dose is working for you.
- ELESTRIN should be used at the lowest dose possible for your treatment and only as long as needed. You and your healthcare provider should talk regularly (for example, every 3 to 6 months) about the dose you are taking and whether you still need treatment with ELESTRIN.
- ELESTRIN comes in a metered-dose pump. One dose of ELESTRIN is released each time the pump is depressed (pressed down).
- Use ELESTRIN exactly how your healthcare provider tells you.
- The ELESTRIN pump contains enough of the medicine to let you prime the pump (get the pump ready) before you use it the first time. To prime the pump, push the head of the pump down slowly, then remove your finger from the pump head and allow it to spring back automatically (by itself). Repeat this until the gel comes out. Throw away this first amount of gel as it will not be a full dose. Once the pump head has come all the way back up, the pump is now primed and ready to use. With each dose, remember to push the pump head down slowly and allow it to spring back automatically. Let the pump head come all the way back up before you push it down again. If using more than 1 dose, wait 5 seconds before pumping the next dose. This will make sure that the pump works correctly and gives your full dose of ELESTRIN. Use the pump a total of 30 times (30 pushes) as your healthcare provider tells you. After you have initially primed the pump and have used a total of 30 doses of ELESTRIN, you will need to throw the pump away and use a new one. The correct amount of medicine in each dose cannot be assured after 30 doses have been used, even though the pump container is not completely empty.

Important things to remember when using ELESTRIN

- Wash your hands with soap and water after applying the gel to reduce the chance that the medicine will be spread from your hands to other people.
- Allow the gel to dry for five minutes or more before dressing. Try to keep the area dry for as long as possible.
- Do not allow others to come in contact with the area of skin where you applied the gel for at least two hours after you apply ELESTRIN.
- Always move the spout into locked position and place the cap over the top of the pump after each use.
- Never apply ELESTRIN to the breast. Never apply ELESTRIN in or around the vagina.
- Do not allow others to apply the gel for you.
- Do not apply sunscreen to the area where the gel was applied for at least 25 minutes.
- Do not apply sunscreen to the area where the gel was applied for 7 or more consecutive days.
- Avoid fire, flame or smoking until the gel has dried. ELESTRIN contains alcohol. Alcohol based gels are flammable.
- It is important that you read and follow the detailed “Patient Instructions for Use” at the end of this leaflet on how to use the ELESTRIN pump and apply the dose.

What should I do if someone else is exposed to ELESTRIN?

If someone else is exposed to ELESTRIN by direct contact with the gel, that person should wash the area of contact with soap and water as soon as possible. The longer the gel is in contact with the skin before washing, the greater is the chance that the other person will absorb some of the estrogen hormone. This is especially important for men and children.

What should I do if I get ELESTRIN in my eyes?

If you get ELESTRIN in your eyes, rinse your eyes right away with warm clean water to flush out any ELESTRIN. Seek medical attention if needed.

What should I do if I miss a dose?

If you miss a dose, do not double the dose on the next day to catch up. If your next dose is less than 12 hours away, it is best just to wait and apply your normal dose the next day. If it is more than 12 hours until the next dose, apply the dose you missed and resume your normal dosing the next day.

What are the possible side effects of ELESTRIN?

Side effects are grouped by how serious they are and how often they happen when you are treated.

Serious, but less common side effects include:

- Heart attack
- Stroke
- Blood clots
- Cancer of the lining of the uterus (womb)
- Breast cancer
- Cancer of the ovary
- Dementia
- Gallbladder disease
- High or low blood calcium

- Visual abnormalities
- High blood pressure
- High levels of fat (triglyceride) in your blood
- Liver problems
- Changes in your thyroid levels
- Fluid retention
- Cancer change of endometriosis
- Enlargement of benign tumors of the uterus (“fibroids”)
- Worsening of swelling of the face and tongue (angioedema) in women with a history of angioedema

Call your healthcare provider right away if you get any of the following warning signs or any other unusual symptoms that concern you:

- New breast lumps
- Unusual vaginal bleeding
- Changes in vision or speech
- Sudden new severe headaches
- Severe pains in your chest or legs with or without shortness of breath, weakness and fatigue

Common side effects of ELESTRIN include:

- Irregular vaginal bleeding or spotting
- Nausea and vomiting
- Vaginal yeast infection
- Headache

- Stomach or abdominal cramps, bloating
- Breast pain
- Hair loss
- Fluid retention

These are not all the possible side effects of ELESTRIN. For more information, ask your healthcare provider or pharmacist. You may report side effects to Meda Pharmaceuticals Inc. at 1-877-999-8401 or to FDA at 1-800-FDA-1088.

What can I do to lower my chances of a serious side effect with ELESTRIN?

- Talk with your healthcare provider regularly about whether you should continue using ELESTRIN
- If you have a uterus, talk to your healthcare provider about whether the addition of a progestin is right for you.
  The addition of a progestin is generally recommended for a woman with a uterus to reduce the chance of getting cancer of the uterus (womb).
- See your healthcare provider right away if you get vaginal bleeding while using ELESTRIN.
- Have a pelvic exam, breast exam and mammogram (breast X-ray) every year unless your healthcare provider tells you something else.
  If members of your family have had breast cancer or if you have ever had breast lumps or an abnormal mammogram, you may need to have breast exams more often.
- If you have high blood pressure, high cholesterol (fat in the blood), diabetes, are overweight, or if you use tobacco, you may have a higher chance for getting heart disease
  Ask your healthcare provider for ways to lower your chances of getting heart disease.

General information about safe and effective use of ELESTRIN

Medicines are sometimes prescribed for conditions that are not mentioned in patient information leaflets. Do not use ELESTRIN for conditions for which it was not prescribed. Do not give ELESTRIN to other people, even if they have the same symptoms you have. It may harm them.

Keep ELESTRIN out of the reach of children

This leaflet provides a summary of the most important information about ELESTRIN. If you would like more information, talk with your healthcare provider or pharmacist. You can ask for information about ELESTRIN that is written for health professionals. You can get more information by calling 1-877-999-8401 (toll free).

What are the ingredients in ELESTRIN?

Active ingredient: estradiol.

Inactive ingredients: purified water, ethanol, propylene glycol, diethylene glycol monoethyl ether, carbomer homopolymer type C, triethanolamine, and edetate disodium.

INSTRUCTIONS FOR USE

ELESTRIN® (el-LES-strin)
(estradiol gel)

1. Remove the cap.
2. Activate the pump.
3. Unlock the pump by turning the spout on top of the bottle a quarter turn to the left or the right.
3. Prime the pump (get the pump ready) before using the pump for the first time.
5. Push the head of the pump down slowly and allow it to spring back automatically. Repeat this until gel comes out. Throw away the first amount of gel as it will not be a full dose. Once the pump head has come all the way back up, the pump is now primed and ready to use. Throw away the unused gel by placing it in the trash to avoid another person or pet from accidental contact with the gel or, eating or drinking it.
6. After priming, the pump is ready to use.
7. One complete pump depression will dispense the same amount of ELESTRIN each time. After each daily dose, return the spout to the locked position and replace the cap before you put it away.
4. Apply ELESTRIN.
9. Dry skin completely before applying ELESTRIN
  You should apply your daily dose of gel to clean, dry, unbroken skin. If you take a bath or shower or use a sauna, apply ELESTRIN after your bath, shower, or sauna. If you go swimming, try to leave as much time as possible, at least 2 hours, between applying your ELESTRIN dose and going into the water.
10. Apply ELESTRIN at the same time each day.

Figure 1

To apply the dose, hold the pump with the tip facing the application area of the arm. For each pump depression needed, press the pump firmly and fully with a continuous motion without hesitation.

Figure 2

Gently spread the gel using only 2 fingers. Spread and gently rub in the gel over the entire area of your upper arm and shoulder area, as illustrated.

5. Wash your hands with soap and water.

ELESTRIN should not be used after the date printed on the container (expiration date).

What are the ingredients in ELESTRIN?

Active ingredient: estradiol.

Inactive ingredients: purified water, ethanol, propylene glycol, diethylene glycol monoethyl ether, carbomer homopolymer type C, triethanolamine, and edetate disodium.

ELESTRIN is a registered trademark of Meda Pharma S.A.R.L., a Viatris Company.

Distributed by:
MEDA Pharmaceuticals Inc.
Canonsburg, PA 15317 U.S.A.
© 2024 Viatris Inc.

Rev. 12/2023
IN-0480-08
141343-1223

PRINCIPAL DISPLAY PANEL – 0.06%

NDC 0037-4801-70

Elestrin®
(estradiol gel) 0.06%
0.52 mg of estradiol per pump actuation*

FOR TOPICAL USE ONLY

Total Contents: 35g x 2

Rx Only

Metered dose pump
container delivering
26 grams gel as
30 metered actuations.

*Each actuation delivers 0.87g of gel

Attention pharmacist:
Dispense with enclosed
Patient Information leaflet.

Important:
Read accompanying
directions carefully.

Contents:
Each gram of Elestrin®
contains 0.6 mg estradiol in a
hydroalcoholic gel containing
purified water, ethanol, propylene
glycol, diethylene glycol monoethyl
ether, carbomer homopolymer type C,
triethanolamine
and edetate disodium.

Usual Dose:
Apply 1 or 2 actuations per day to
upper arm/shoulder area as directed
by your physician. See enclosed
Prescribing Information.

The metered dose pump
must be primed before first use.
After initial priming, each actuation
delivers 0.87 grams of gel which
contains 0.52 mg of estradiol.

Net weight 35 grams
per pump container

WARNINGS

Keep out of the reach of children;
this container is not child-resistant.

Gels are flammable. Avoid fire,
flame, or smoking during application.

Store at 20º to 25ºC (68º to 77ºF);
excursions permitted to
15º to 30ºC (59º to 86ºF)

Distributed by:
Meda
Pharmaceuticals®
Canonsburg, PA 15317 U.S.A.

© 2024 Viatris Inc.

www.meda.us
www.elestrin.com

MEDA PHARMACEUTICALS and the
Meda Pharmaceuticals Logo are
trademarks of Meda AB,
a Viatris Company.

UC-048002-06

Rev. 05/2024